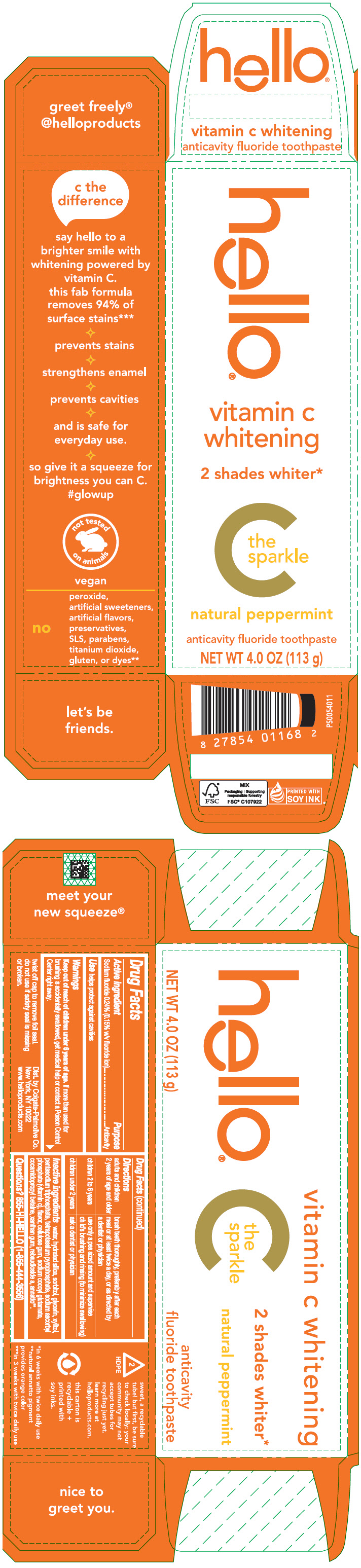 DRUG LABEL: Hello Vitamin C Whitening
NDC: 35000-689 | Form: PASTE, DENTIFRICE
Manufacturer: Colgate-Palmolive Company
Category: otc | Type: HUMAN OTC DRUG LABEL
Date: 20231120

ACTIVE INGREDIENTS: SODIUM FLUORIDE 1.5 mg/1 g
INACTIVE INGREDIENTS: WATER; HYDRATED SILICA; SORBITOL; GLYCERIN; XYLITOL; SODIUM TRIPOLYPHOSPHATE ANHYDROUS; SODIUM PYROPHOSPHATE; SODIUM ASCORBYL PHOSPHATE; CARBOXYMETHYLCELLULOSE SODIUM, UNSPECIFIED; SODIUM COCOYL GLUTAMATE; COCAMIDOPROPYL BETAINE; XANTHAN GUM; REBAUDIOSIDE A; ANNATTO

Hello® Vitamin C Whitening

Drug Facts

Active ingredient

Sodium fluoride 0.24% (0.15% w/v fluoride ion)

Purpose

Anticavity

Use

helps protect against cavities

Warnings

Keep out of reach of children under 6 years of age. If more than used for brushing is accidentally swallowed, get medical help or contact a Poison Control Center right away.

Directions

adults and children 2 years of age and older | brush teeth thoroughly, preferably after each meal or at least twice a day, or as directed by a dentist or physician
chldren 2 to 6 years | use only a pea sized amount and supervise child's brushing and rinsing (to minimize swallowing)
children under 2 years | ask a dentist or physician

Inactive ingredients

water, hydrated silica, sorbitol, glycerin, xylitol, pentasodium triphosphate, tetrapotassium pyrophosphate, sodium ascorbyl phosphate (vitamin c), flavor, cellulose gum, sodium cocoyl glutamate, cocamidopropyl betaine, xanthan gum, rebaudioside a, annatto [natural annatto pigment provides orange color] .

Questions?

855-HI-HELLO (1-855-444-3556)

Dist. by Colgate-Palmolive Co.
New York, NY 10022

PRINCIPAL DISPLAY PANEL - 113 g Tube Carton

hello®

vitamin c
whitening

2 shades whiter*

C
the
sparkle

natural peppermint

anticavity fluoride toothpaste

NET WT 4.0 OZ (113 g)